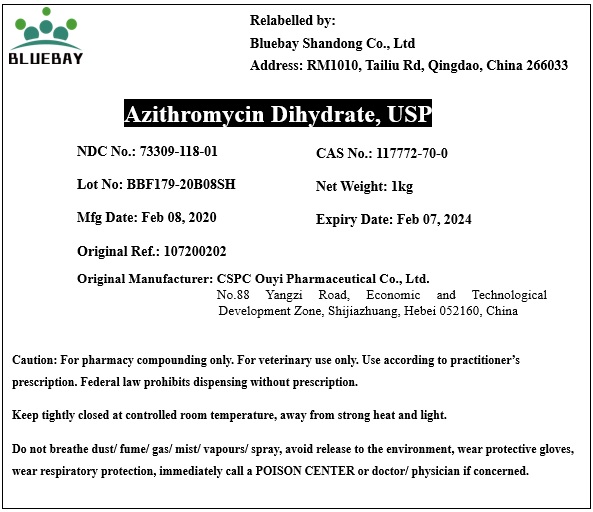 DRUG LABEL: Azithromycin Dihydrate
NDC: 73309-118 | Form: POWDER
Manufacturer: BLUEBAY SHANDONG CO.,LTD
Category: other | Type: BULK INGREDIENT
Date: 20200414

ACTIVE INGREDIENTS: AZITHROMYCIN DIHYDRATE 1 kg/1 kg

Azithromycin Dihydrate